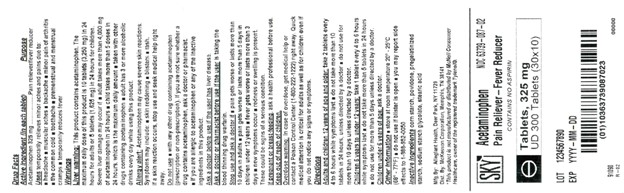 DRUG LABEL: Acetaminophen 325mg
NDC: 63739-087 | Form: TABLET
Manufacturer: McKesson Corporation dba SKY Packaging
Category: otc | Type: HUMAN OTC DRUG LABEL
Date: 20241220

ACTIVE INGREDIENTS: ACETAMINOPHEN 325 mg/1 1
INACTIVE INGREDIENTS: STARCH, CORN; POVIDONE; SODIUM STARCH GLYCOLATE TYPE A CORN; STEARIC ACID

Drug Facts

Active Ingredient (in each tablet)

Acetaminophen 325mg

Purpose

Pain reliever/fever reducer

Uses

temporary relief of minor aches and pains associated with:

- headache
- backache
- muscular aches
- minor pain of arthritis
- the common cold
- toothache
- premenstrual and menstrual cramps
- temporarily reduces fever

Warnings

Liver Warning: This product contains acetaminophen. Severe liver damage may occur if

- adult takes more than 4,000 mg in 24 hours
- child takes more than 5 doses in 24 hours
- taken with other drugs containing acetaminophen
- adult has 3 or more alcoholic drinks every day while using this product

Allergy alert: Acetaminophen may cause severe skin reactions. Symptoms may include:

- skin reddening
- blisters
- rash

If a skin reaction occurs, stop use and seek medical help right away.

Do not use

- if you are allergic to acetamiophen
- with other products containing acetaminophen (prescription or nonprescription).

If you are not sure whether a drug contains acetaminophen, ask a doctor or pharmacist.

Ask a doctor before use if user has

liver disease.

Ask a doctor or pharmacist before use if

the user is taking the blood thinning drug warfarin

Stop use and ask a doctor if

- symptoms do not improve
- pain gets worse or lasts for more than 10 days
- pain gets worse or lasts more than 5 days in children under 12 years
- fever gets worse or lasts for more than 3 days
- new symptoms occur
- redness or swelling is present
- a rare sensitivity reaction occurs
- You may report side effects to 1-888-952-0050

If pregnant or breast-feeding, ask a health professional before use.

Keep out of reach of children. In case of accidental overdose, contact a doctor or Poison Control Center immediately. Prompt medical attention is critical for adults as well as for children even if you do not notice any signs or symptoms.

Directions

Adults and children 12 years of age and over: Take 2 tablets every 4 to 6 hours.

Do not take more than 10 tablets in 24 hours.

Children 6-11 years of age: Take 1 tablet every 4 to 6 hours as needed.

Do not take more than 5 tablets in 24 hours.

Children under 6 years of age: Do not use this regular strenght product. This will provide more than the recommended dose (overdose) and could cause serious health problems.

Other information

- store at room temperature
- do not use if imprinted safety seal under cap is broken or missing

Inactive ingredients

corn starch, povidone, pregelatinized starch, sodium starch glycolate, stearic acid